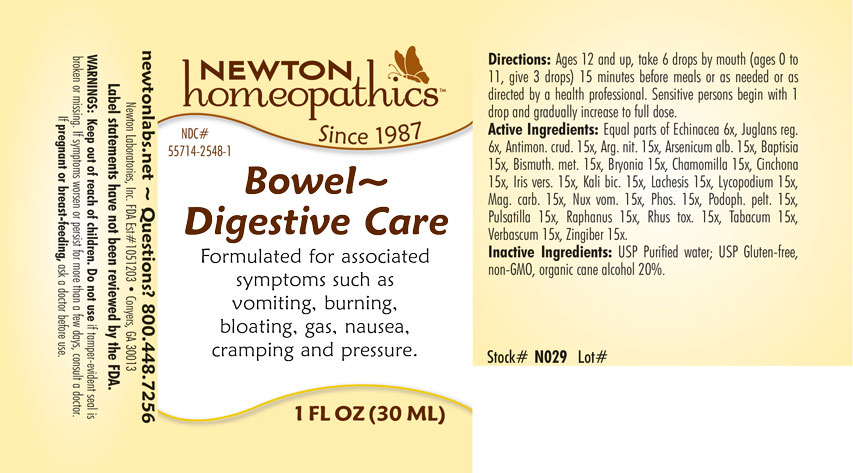 DRUG LABEL: Bowel - Digestive Care
NDC: 55714-2548 | Form: LIQUID
Manufacturer: Newton Laboratories, Inc.
Category: homeopathic | Type: HUMAN OTC DRUG LABEL
Date: 20241024

ACTIVE INGREDIENTS: BISMUTH 15 [hp_X]/1 mL; ANTIMONY TRISULFIDE 15 [hp_X]/1 mL; SILVER NITRATE 15 [hp_X]/1 mL; ARSENIC TRIOXIDE 15 [hp_X]/1 mL; BAPTISIA TINCTORIA 15 [hp_X]/1 mL; BRYONIA ALBA ROOT 15 [hp_X]/1 mL; MATRICARIA RECUTITA 15 [hp_X]/1 mL; CINCHONA OFFICINALIS BARK 15 [hp_X]/1 mL; IRIS VERSICOLOR ROOT 15 [hp_X]/1 mL; POTASSIUM DICHROMATE 15 [hp_X]/1 mL; LACHESIS MUTA VENOM 15 [hp_X]/1 mL; LYCOPODIUM CLAVATUM SPORE 15 [hp_X]/1 mL; MAGNESIUM CARBONATE 15 [hp_X]/1 mL; STRYCHNOS NUX-VOMICA SEED 15 [hp_M]/1 mL; PHOSPHORUS 15 [hp_X]/1 mL; PODOPHYLLUM 15 [hp_X]/1 mL; PULSATILLA VULGARIS 15 [hp_X]/1 mL; RADISH 15 [hp_X]/1 mL; TOXICODENDRON PUBESCENS LEAF 15 [hp_X]/1 mL; TOBACCO LEAF 15 [hp_X]/1 mL; VERBASCUM THAPSUS 15 [hp_X]/1 mL; GINGER 15 [hp_X]/1 mL; ECHINACEA, UNSPECIFIED 6 [hp_X]/1 mL; ENGLISH WALNUT 6 [hp_X]/1 mL
INACTIVE INGREDIENTS: WATER; ALCOHOL

Bowel 2548L

DOSAGE & ADMINISTRATION SECTION

Directions: Ages 12 and up, take 6 drops by mouth (ages 0 to 11, give 3 drops) 15 minutes before meals or as needed or as directed by a health professional. Sensitive persons begin with 1 drop and gradually increase to full dose.

INDICATIONS & USAGE SECTION

Formulated for associated symptoms such as vomiting, burning, bloating, gas, nausea, cramping and pressure.

OTC - KEEP OUT OF REACH OF CHILDREN SECTION

Keep out of reach of children.

OTC - PREGNANCY OR BREAST FEEDING SECTION

If pregnant or breast feeding, ask a doctor before use.

WARNINGS SECTION

WARNINGS: Keep out of reach of children. Do not use if tamper-evident seal is broken or missing. If symptoms worsen or persist for more than a few days, consult a doctor. If pregnant or breast-feeding, ask a doctor before use.

QUESTIONS SECTION

newtonlabs.net - Questions? 800 448-7256

Newton Laboratories, Inc. FDA Est # 1051203 - Conyers, GA 30013

INACTIVE INGREDIENT SECTION

Inactive Ingredients: USP Purified Water; USP Gluten-free, non-GMO, organic cane alcohol 20%.

OTC - PURPOSE SECTION

Formulated for associated symptoms such as vomiting, burning, bloating, gas, nausea, cramping and pressure.

OTC - ACTIVE INGREDIENT SECTION

Equal parts of Echinacea 6x, Juglans reg. 6x, Antimon.crud. 15x, Arg. nit. 15x, Arsenicum alb. 15x, Baptisia 15x, Bismuth. met. 15x, Bryonia 15x, Chamomilla 15x, Cinchona 15x, Iris vers. 15x, Kali bic. 15x, Lachesis 15x, Lycopodium 15x, Mag. carb. 15x, Nux vom. 15x, Phos. 15x, Podoph. pelt. 15x, Pulsatilla 15x, Raphanus 15x, Rhus tox. 15x, Tabacum 15x, Verbascum 15x, Zingiber 15x.